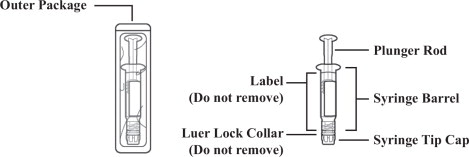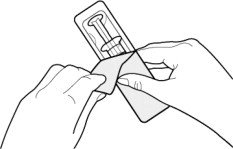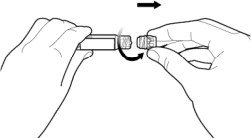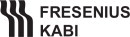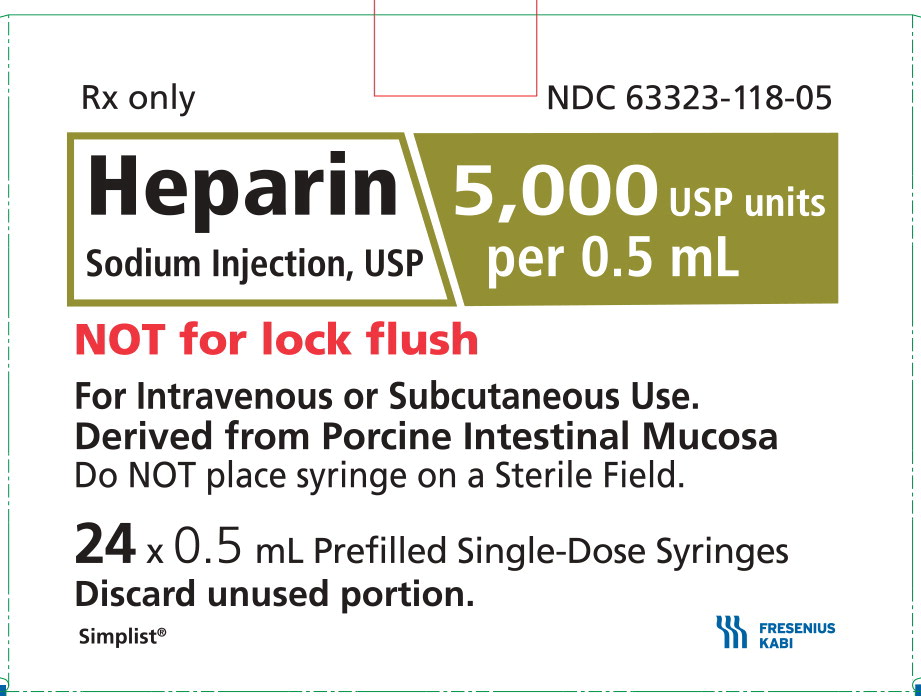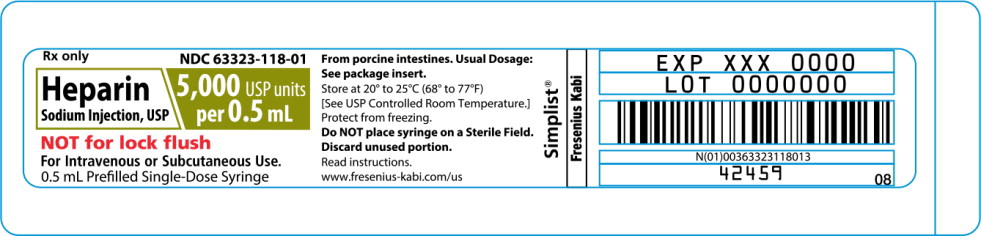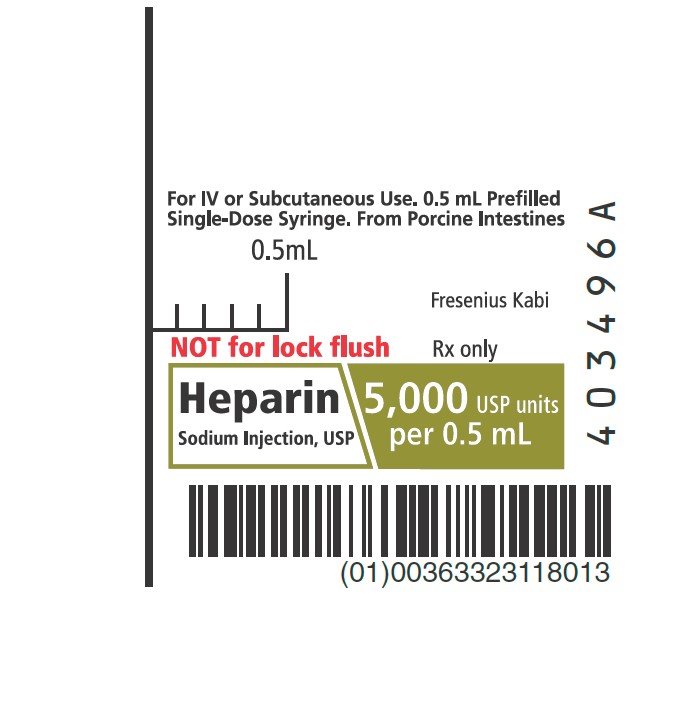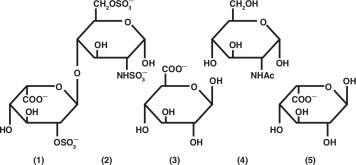 DRUG LABEL: Heparin Sodium
NDC: 63323-118 | Form: INJECTION, SOLUTION
Manufacturer: Fresenius Kabi USA, LLC
Category: prescription | Type: HUMAN PRESCRIPTION DRUG LABEL
Date: 20250815

ACTIVE INGREDIENTS: Heparin Sodium 5000 [USP'U]/0.5 mL
INACTIVE INGREDIENTS: Sodium Chloride; Sodium Hydroxide; Hydrochloric Acid; Water

HIGHLIGHTS OF PRESCRIBING INFORMATION

These highlights do not include all the information needed to use HEPARIN SODIUM INJECTION safely and effectively. See full prescribing information for HEPARIN SODIUM INJECTION.
HEPARIN SODIUM INJECTION, for intravenous or subcutaneous use Initial U.S. Approval: 1939

1 INDICATIONS AND USAGE

HEPARIN SODIUM INJECTION is an anticoagulant indicated for (1)

- Prophylaxis and treatment of venous thrombosis and pulmonary embolism
- Prevention of postoperative deep venous thrombosis and pulmonary embolism in patients undergoing major abdominothoracic surgery or who, for other reasons, are at risk of developing thromboembolic disease
- Atrial fibrillation with embolization
- Treatment of acute and chronic consumptive coagulopathies (disseminated intravascular coagulation)
- Prevention of clotting in arterial and cardiac surgery
- Prophylaxis and treatment of peripheral arterial embolism
- Use as an anticoagulant in blood transfusions, extracorporeal circulation, and dialysis procedures

2 DOSAGE AND ADMINISTRATION

Recommended Adult Dosages:

- Therapeutic Anticoagulant Effect with Full-Dose Heparin† (2.3)

Deep Subcutaneous (Intrafat) Injection Use a different site for each injection | Initial Dose | 5,000 units by intravenous injection, followed by 10,000 units to 20,000 units of a concentrated solution, subcutaneously
Deep Subcutaneous (Intrafat) Injection Use a different site for each injection | Every 8 hours or Every 12 hours | 8,000 units to 10,000 units of a concentrated solution 15,000 units to 20,000 units of a concentrated solution
Intermittent Intravenous Injection | Initial dose | 10,000 units, either undiluted or in 50 mL to 100 mL of 0.9% Sodium Chloride Injection, USP by intravenous injection
Intermittent Intravenous Injection | Every 4 to 6 hours | 5,000 units to 10,000 units, either undiluted or in 50 mL to 100 mL of 0.9% Sodium Chloride Injection, USP
Intravenous Infusion | Initial dose | 5,000 units by intravenous injection
Intravenous Infusion | Continuous | 20,000 units/24 hours to 40,000 units/24 hours in 1,000 mL of 0.9% Sodium Chloride Injection, USP (or in any compatible solution) for infusion
† Based on 68 kg patient. Adjust dose based on laboratory monitoring.

3 DOSAGE FORMS AND STRENGTHS

Injection: 5,000 USP units per 0.5 mL (10,000 USP units/mL) preservative-free clear solution in prefilled single-dose syringe

4 CONTRAINDICATIONS

- Severe thrombocytopenia (4)
- When suitable blood coagulation tests, e.g., the whole blood clotting time, partial thromboplastin time, etc., cannot be performed at appropriate intervals (4)
- An uncontrolled active bleeding state, except when this is due to disseminated intravascular coagulation (4)

5 WARNINGS AND PRECAUTIONS

- Fatal Medication Errors: Confirm choice of correct strength prior to administration (5.1)
- Hemorrhage: Fatal cases have occurred. Use caution in conditions with increased risk of hemorrhage (5.2)
- HIT and HITT: Monitor for signs and symptoms and discontinue if indicative of HIT and HITT (5.3)
- Monitoring: Blood coagulation tests guide therapy for full-dose heparin.
- Monitor platelet count and hematocrit in all patients receiving heparin (5.5, 5.6)

6 ADVERSE REACTIONS

Most common adverse reactions are hemorrhage, thrombocytopenia, HIT and HITT, injection site irritation, general hypersensitivity reactions, and elevations of aminotransferase levels. (6.1)

To report SUSPECTED ADVERSE REACTIONS, contact Fresenius Kabi USA, LLC at 1-800-551-7176 or FDA at 1-800-FDA-1088 or www.fda.gov/medwatch.

7 DRUG INTERACTIONS

Drugs that interfere with platelet aggregation: May induce bleeding (7.2)

8 USE IN SPECIFIC POPULATIONS

- Pregnancy: Limited human data in pregnant women. (8.1)
- Lactation: Advise females not to breastfeed. (8.2)
- Geriatric Use: A higher incidence of bleeding reported in patients, particularly women, over 60 years of age. (8.5)

FULL PRESCRIBING INFORMATION

1 INDICATIONS AND USAGE

Heparin Sodium Injection is indicated for:

- Prophylaxis and treatment of venous thrombosis and pulmonary embolism;
- Prevention of postoperative deep venous thrombosis and pulmonary embolism in patients undergoing major abdominothoracic surgery or who, for other reasons, are at risk of developing thromboembolic disease;
- Atrial fibrillation with embolization;
- Treatment of acute and chronic consumptive coagulopathies (disseminated intravascular coagulation);
- Prevention of clotting in arterial and cardiac surgery;
- Prophylaxis and treatment of peripheral arterial embolism.
- Anticoagulant use in blood transfusions, extracorporeal circulation, and dialysis procedures.

2 DOSAGE AND ADMINISTRATION

2.1 Preparation for Administration

Confirm the choice of the correct Heparin Sodium Injection syringe to ensure that the 1 mL syringe is not confused with a “catheter lock flush” syringe or other 1 mL syringe of incorrect strength [see Warnings and Precautions (5.1)]. Confirm the selection of the correct formulation and strength prior to administration of the drug.

When heparin is added to an infusion solution for continuous intravenous administration, invert the container repeatedly to ensure adequate mixing and prevent pooling of the heparin in the solution. Visually inspect parenteral drug products for particulate matter and discoloration prior to administration, whenever solution and container permit. Use only if solution is clear and the seal is intact. Do not use if solution is discolored or contains a precipitate.

Administer Heparin Sodium Injection by intermittent intravenous injection, intravenous infusion, or deep subcutaneous (intrafat, i.e., above the iliac crest or abdominal fat layer) injection. Do not administer Heparin Sodium Injection by intramuscular injection because of the risk of hematoma at the injection site [see Adverse Reactions (6)].

2.2 Laboratory Monitoring for Efficacy and Safety

Adjust the dosage of Heparin Sodium Injection according to the patient's coagulation test results. Dosage is considered adequate when the activated partial thromboplastin time (aPTT) is 1.5 to 2 times normal or when the whole blood clotting time is elevated approximately 2.5 to 3 times the control value. When initiating treatment with Heparin Sodium Injection by continuous intravenous infusion, determine the coagulation status (aPTT, INR, platelet count) at baseline and continue to follow aPTT approximately every 4 hours and then at appropriate intervals thereafter. When the drug is administered intermittently by intravenous injection, perform coagulation tests before each injection during the initiation of treatment and at appropriate intervals thereafter. After deep subcutaneous (intrafat) injections, tests for adequacy of dosage are best performed on samples drawn 4 to 6 hours after the injection.

Periodically monitor platelet counts and hematocrits during the entire course of heparin therapy, regardless of the route of administration.

2.3 Therapeutic Anticoagulant Effect with Full-Dose Heparin

The dosing recommendations in Table 1 are based on clinical experience. Although dosages must be adjusted for the individual patient according to the results of suitable laboratory tests, the following dosage schedules may be used as guidelines:

Table 1: Recommended Adult Full-Dose Heparin Regimens for Therapeutic Anticoagulant Effect
METHOD OF ADMINISTRATION | FREQUENCY | RECOMMENDED DOSE [based on 68 kg patient]
Deep Subcutaneous (Intrafat) Injection A different site should be used for each injection to prevent development of massive hematoma | Initial Dose | 5,000 units by intravenous injection, followed by 10,000 units to 20,000 units of a concentrated solution, subcutaneously
Deep Subcutaneous (Intrafat) Injection A different site should be used for each injection to prevent development of massive hematoma | Every 8 hours Or Every 12 hours | 8,000 units to 10,000 units of a concentrated solution 15,000 units to 20,000 units of a concentrated solution
Intermittent Intravenous Injection | Initial Dose | 10,000 units, either undiluted or in 50 mL to 100 mL of 0.9% Sodium Chloride Injection, USP by intravenous injection
Intermittent Intravenous Injection | Every 4 to 6 hours | 5,000 units to 10,000 units, either undiluted or in 50 mL to 100 mL of 0.9% Sodium Chloride Injection, USP
Intravenous Infusion | Initial Dose | 5,000 units by intravenous injection
Intravenous Infusion | Continuous | 20,000 units/24 hours to 40,000 units/24 hours in 1,000 mL of 0.9% Sodium Chloride Injection, USP (or in any compatible solution) for infusion

2.4 Cardiovascular Surgery

Patients undergoing total body perfusion for open-heart surgery should receive an initial dose of not less than 150 units of heparin sodium per kilogram of body weight. Frequently, a dose of 300 units per kilogram is used for procedures estimated to last less than 60 minutes, or 400 units per kilogram for those estimated to last longer than 60 minutes.

2.5 Low-Dose Prophylaxis of Postoperative Thromboembolism

The most widely used dosage has been 5,000 units 2 hours before surgery and 5,000 units every 8 to 12 hours thereafter for 7 days or until the patient is fully ambulatory, whichever is longer. Administer the heparin by deep subcutaneous (intrafat, i.e., above the iliac crest or abdominal fat layer, arm, or thigh) injection with a fine (25 to 26-gauge) needle to minimize tissue trauma.

2.6 Blood Transfusion

Add 450 USP units to 600 USP units of heparin sodium per 100 mL of whole blood to prevent coagulation. Usually, 7,500 USP units of heparin sodium are added to 100 mL of 0.9% Sodium Chloride Injection, USP (or 75,000 USP units per 1,000 mL of 0.9% Sodium Chloride Injection, USP) and mixed; from this sterile solution, 6 mL to 8 mL are added per 100 mL of whole blood.

2.7 Converting to Warfarin

To ensure continuous anticoagulation when converting from Heparin Sodium Injection to warfarin, continue full heparin therapy for several days until the INR (prothrombin time) has reached a stable therapeutic range. Heparin therapy may then be discontinued without tapering [see Drug Interactions (7.1)].

2.8 Converting to Oral Anticoagulants other than Warfarin

For patients currently receiving intravenous heparin, stop intravenous infusion of heparin sodium immediately after administering the first dose of oral anticoagulant; or for intermittent intravenous administration of heparin sodium, start oral anticoagulant 0 to 2 hours before the time that the next dose of heparin was to have been administered.

2.9 Extracorporeal Dialysis

Follow equipment manufacturers' operating directions carefully. A dose of 25 units/kg to 30 units/kg followed by an infusion rate of 1,500 units/hour to 2,000 units/hour is suggested based on pharmacodynamic data if specific manufacturers' recommendations are not available.

2.10 Administration Technique

Figure 1: Outer Packaging and Prefilled Syringe

NOTES:

- Do not introduce any other fluid into the syringe at any time.
- Do not dilute for intravenous push.
- Do not re-sterilize the syringe.
- Do not use this product on a sterile field.
- This product is for single dose only.

1. Inspect the outer packaging (blister pack) to confirm the integrity of the packaging. Do not use if the blister pack or the prefilled syringe has been damaged.

2. Remove the syringe from the outer packaging. (See Figure 2)

Figure 2

3. Visually inspect the syringe. Parenteral drug products should be inspected visually for particulate matter and discoloration prior to administration, whenever solution and container permit.

4. Twist off the syringe tip cap. Do not remove the label around the luer lock collar. (See Figure 3)

Figure 3

5. Expel air bubble(s). Adjust the dose (if applicable).

6. Administer the dose ensuring that pressure is maintained on the plunger rod during the entire administration.

7. Discard the syringe into the appropriate receptacle.

3 DOSAGE FORMS AND STRENGTHS

Heparin Sodium Injection, USP is available as:

- Injection: 5,000 USP units per 0.5 mL (10,000 USP units/mL) preservative-free clear solution in a prefilled single-dose syringe.

4 CONTRAINDICATIONS

The use of Heparin Sodium Injection is contraindicated in patients with the following conditions:

- History of heparin-induced thrombocytopenia and heparin-induced thrombocytopenia and thrombosis [see Warnings and Precautions (5.3)];
- Known hypersensitivity to heparin or pork products (e.g., anaphylactoid reactions) [see Adverse Reactions (6.1)]
- In whom suitable blood coagulation tests, e.g., the whole blood clotting time, partial thromboplastin time, etc., cannot be performed at appropriate intervals (this contraindication refers to full-dose heparin; there is usually no need to monitor coagulation parameters in patients receiving low-dose heparin);
- An uncontrolled active bleeding state [see Warnings and Precautions (5.4)], except when this is due to disseminated intravascular coagulation.

5 WARNINGS AND PRECAUTIONS

5.1 Fatal Medication Errors

Do not use Heparin Sodium Injection as a “catheter lock flush” product. Heparin Sodium Injection is supplied in syringes containing a highly concentrated solution of 10,000 units in 1 mL (5,000 units per 0.5 mL). Fatal hemorrhages have occurred in pediatric patients due to medication errors in which 1 mL Heparin Sodium Injection vials were confused with 1 mL “catheter lock flush” vials. Carefully examine all Heparin Sodium Injection syringes to confirm the correct syringe choice prior to administration of the drug.

5.2 Hemorrhage

Avoid using heparin in the presence of major bleeding, except when the benefits of heparin therapy outweigh the potential risks.

Hemorrhage can occur at virtually any site in patients receiving heparin. Fatal hemorrhages have occurred. Adrenal hemorrhage (with resultant acute adrenal insufficiency), ovarian hemorrhage, and retroperitoneal hemorrhage have occurred during anticoagulant therapy with heparin [see Adverse Reactions (6.1)]. A higher incidence of bleeding has been reported in patients, particularly women, over 60 years of age [see Clinical Pharmacology (12.3)]. An unexplained fall in hematocrit, fall in blood pressure or any other unexplained symptom should lead to serious consideration of a hemorrhagic event.

Use heparin sodium with caution in disease states in which there is increased risk of hemorrhage, including:

- Cardiovascular - Subacute bacterial endocarditis, severe hypertension.
- Surgical - During and immediately following (a) spinal tap or spinal anesthesia or (b) major surgery, especially involving the brain, spinal cord, or eye.
- Hematologic - Conditions associated with increased bleeding tendencies, such as hemophilia, thrombocytopenia and some vascular purpuras.
- Patients with hereditary antithrombin III deficiency receiving concurrent antithrombin III therapy
  - The anticoagulant effect of heparin is enhanced by concurrent treatment with antithrombin III (human) in patients with hereditary antithrombin III deficiency. To reduce the risk of bleeding, reduce the heparin dose during concomitant treatment with antithrombin III (human).
- Gastrointestinal - Ulcerative lesions and continuous tube drainage of the stomach or small intestine.
- Other - Menstruation, liver disease with impaired hemostasis.

5.3 Heparin-Induced Thrombocytopenia and Heparin-Induced Thrombocytopenia and Thrombosis

Heparin-induced thrombocytopenia (HIT) is a serious antibody-mediated reaction. HIT occurs in patients treated with heparin and is due to the development of antibodies to a platelet Factor 4-heparin complex that induce in vivo platelet aggregation. HIT may progress to the development of venous and arterial thromboses, a condition referred to as heparin-induced thrombocytopenia with thrombosis (HITT). Thrombotic events may also be the initial presentation for HITT. These serious thromboembolic events include deep vein thrombosis, pulmonary embolism, cerebral vein thrombosis, limb ischemia, stroke, myocardial infarction, mesenteric thrombosis, renal arterial thrombosis, skin necrosis, gangrene of the extremities that may lead to amputation, and possibly death. If the platelet count falls below 100,000/mm^3 or if recurrent thrombosis develops, promptly discontinue heparin, evaluate for HIT and HITT, and, if necessary, administer an alternative anticoagulant. HIT or HITT can occur up to several weeks after the discontinuation of heparin therapy. Patients presenting with thrombocytopenia or thrombosis after discontinuation of heparin sodium should be evaluated for HIT or HITT.

5.4 Thrombocytopenia

Thrombocytopenia in patients receiving heparin has been reported at frequencies up to 30%. It can occur 2 to 20 days (average 5 to 9) following the onset of heparin therapy. Obtain platelet counts before and periodically during heparin therapy. Monitor thrombocytopenia of any degree closely. If the count falls below 100,000/mm^3 or if recurrent thrombosis develops, promptly discontinue heparin, evaluate for HIT and HITT, and, if necessary, administer an alternative anticoagulant [see Warnings and Precautions (5.3)].

5.5 Coagulation Testing and Monitoring

When using a full dose heparin regimen, adjust the heparin dose based on frequent blood coagulation tests. If the coagulation test is unduly prolonged or if hemorrhage occurs, discontinue heparin promptly [see Overdosage (10)]. Periodic platelet counts and hematocrits are recommended during the entire course of heparin therapy, regardless of the route of administration [see Dosage and Administration (2.2)].

5.6 Heparin Resistance

Resistance to heparin is frequently encountered in fever, thrombosis, thrombophlebitis, infections with thrombosing tendencies, myocardial infarction, cancer, in postsurgical patients, and patients with antithrombin III deficiency. Close monitoring of coagulation tests is recommended in these cases. Adjustment of heparin doses based on anti-Factor Xa levels may be warranted.

5.7 Hypersensitivity

Patients with documented hypersensitivity to heparin should be given the drug only in clearly life- threatening situations.

Because Heparin Sodium Injection is derived from animal tissue, it should be used with caution in patients with a history of allergy.

6 ADVERSE REACTIONS

The following clinically significant adverse reactions are described elsewhere in the labeling:

- Hemorrhage [see Warnings and Precautions (5.2)]
- Heparin-Induced Thrombocytopenia and Heparin-Induced Thrombocytopenia and Thrombosis [see Warnings and Precautions (5.3)]
- Thrombocytopenia [see Warnings and Precautions (5.4)]
- Heparin Resistance [see Warnings and Precautions (5.6)]
- Hypersensitivity [see Warnings and Precautions (5.7)]

6.1 Postmarketing Experience

The following adverse reactions have been identified during post approval use of Heparin Sodium Injection. Because these reactions are reported voluntarily from a population of uncertain size, it is not always possible to reliably estimate their frequency or establish a causal relationship to drug exposure.

- Hemorrhage is the chief complication that may result from heparin therapy [see Warnings and Precautions (5.2)]. Gastrointestinal or urinary tract bleeding during anticoagulant therapy may indicate the presence of an underlying occult lesion. Bleeding can occur at any site but certain specific hemorrhagic complications may be difficult to detect:
  - Adrenal hemorrhage, with resultant acute adrenal insufficiency, has occurred with heparin therapy, including fatal cases.
  - Ovarian (corpus luteum) hemorrhage developed in a number of women of reproductive age receiving short- or long-term heparin therapy.
  - Retroperitoneal hemorrhage
- HIT and HITT, including delayed onset cases [see Warnings and Precautions (5.3)].
- Local Irritation – Local irritation, erythema, mild pain, hematoma or ulceration may follow deep subcutaneous (intrafat) injection of heparin sodium. Because these complications are much more common after intramuscular use, the intramuscular route is not recommended.
- Histamine-like reactions – Such reactions have been observed at the site of injections. Necrosis of the skin has been reported at the site of subcutaneous injection of heparin, occasionally requiring skin grafting [see Warnings and Precautions (5.3)].
- Hypersensitivity – Generalized hypersensitivity reactions have been reported, with chills, fever and urticaria as the most usual manifestations, and asthma, rhinitis, lacrimation, headache, nausea and vomiting, and anaphylactoid reactions, including shock, occurring less frequently. Itching and burning, especially on the plantar side of the feet, may occur. [see Warnings and Precautions (5.8)]
- Elevations of aminotransferases – Significant elevations of aspartate aminotransferase (AST) and alanine aminotransferase (ALT) levels have occurred in patients who have received heparin [see Drug Interactions (7.4)].
- Miscellaneous - Osteoporosis following long-term administration of high doses of heparin, cutaneous necrosis after systemic administration, suppression of aldosterone synthesis, delayed transient alopecia, priapism, and rebound hyperlipemia on discontinuation of heparin sodium have also been reported.

7 DRUG INTERACTIONS

7.1 Oral Anticoagulants

Heparin sodium may prolong the one-stage prothrombin time. Therefore, when heparin sodium is given with dicumarol or warfarin sodium, a period of at least 5 hours after the last intravenous dose or 24 hours after the last subcutaneous dose should elapse before blood is drawn, if a valid prothrombin time is to be obtained.

7.2 Platelet Inhibitors

Drugs such as NSAIDS (including salicylic acid, ibuprofen, indomethacin, and celecoxib), dextran, phenylbutazone, thienopyridines, dipyridamole, hydroxychloroquine, glycoprotein IIb/IIIa antagonists (including abciximab, eptifibatide, and tirofiban), and others that interfere with platelet-aggregation reactions (the main hemostatic defense of heparinized patients) may induce bleeding and should be used with caution in patients receiving heparin sodium. To reduce the risk of bleeding, a reduction in the dose of antiplatelet agent or heparin is recommended.

7.3 Other Interactions

Digitalis, tetracyclines, nicotine or antihistamines may partially counteract the anticoagulant action of heparin sodium. Intravenous nitroglycerin administered to heparinized patients may result in a decrease of the partial thromboplastin time with subsequent rebound effect upon discontinuation of nitroglycerin. Careful monitoring of partial thromboplastin time and adjustment of heparin dosage are recommended during coadministration of heparin and intravenous nitroglycerin.

Antithrombin III (human) – The anticoagulant effect of heparin is enhanced by concurrent treatment with antithrombin III (human) in patients with hereditary antithrombin III deficiency. To reduce the risk of bleeding, a reduced dosage of heparin is recommended during treatment with antithrombin III (human).

8 USE IN SPECIFIC POPULATIONS

8.1 Pregnancy

Risk Summary

There are no available data on Heparin Sodium Injection use in pregnant women to inform a drug- associated risk of major birth defects and miscarriage. In published reports, heparin exposure during pregnancy did not show evidence of an increased risk of adverse maternal or fetal outcomes in humans. No teratogenicity, but early embryo-fetal death was observed in animal reproduction studies with administration of heparin sodium to pregnant rats and rabbits during organogenesis at doses approximately 10 times the maximum recommended human dose (MRHD) of 45,000 units/ day (see Data). Consider the benefits and risks of Heparin Sodium Injection for the mother and possible risks to the fetus when prescribing Heparin Sodium Injection to a pregnant woman.

If available, preservative-free Heparin Sodium Injection is recommended when heparin therapy is needed during pregnancy.

The background risk of major birth defects and miscarriage for the indicated population is unknown. All pregnancies have a background risk of birth defect, loss, or other adverse outcomes. In the U.S. general population, the estimated background risk of major birth defects and miscarriage in clinically recognized pregnancies is 2-4% and 15-20%, respectively.

Data

Human Data

The maternal and fetal outcomes associated with uses of heparin via various dosing methods and administration routes during pregnancy have been investigated in numerous studies. These studies generally reported normal deliveries with no maternal or fetal bleeding and no other complications.

Animal Data

In a published study conducted in rats and rabbits, pregnant animals received heparin intravenously during organogenesis at a dose of 10,000 units/kg/day, approximately 10 times the maximum human daily dose based on body weight. The number of early resorptions increased in both species. There was no evidence of teratogenic effects.

8.2 Lactation

Risk Summary

There is no information regarding the presence of Heparin Sodium Injection in human milk, the effects on the breastfed child, or the effects on milk production. Due to its large molecular weight, heparin is not likely to be excreted in human milk, and any heparin in milk would not be orally absorbed by a nursing child. The developmental and health benefits of breastfeeding should be considered along with the mother's clinical need for Heparin Sodium Injection and any potential adverse effects on the breastfed child from Heparin Sodium Injection or from the underlying maternal condition [see Use in Specific Populations (8.4)].

8.4 Pediatric Use

Pediatric dosing is not achievable with the prefilled syringe presentation. Use another heparin product presentation when dosing pediatric patients.

8.5 Geriatric Use

There are limited adequate and well-controlled studies in patients 65 years and older, however, a higher incidence of bleeding has been reported in patients, particularly women, over 60 years of age [see Warnings and Precautions (5.2)]. Patients over 60 years of age may require lower doses of heparin. Lower doses of heparin may be indicated in these patients [see Clinical Pharmacology (12.3)].

10 OVERDOSAGE

Bleeding is the chief sign of heparin overdosage.

Neutralization of Heparin Effect

When clinical circumstances (bleeding) require reversal of the heparin effect, protamine sulfate (1% solution) by slow infusion will neutralize heparin sodium. No more than 50 mg should be administered, very slowly, in any 10-minute period. Each mg of protamine sulfate neutralizes approximately 100 USP heparin units. The amount of protamine required decreases over time as heparin is metabolized. Although the metabolism of heparin is complex, it may, for the purpose of choosing a protamine dose, be assumed to have a half-life of about 1/2 hour after intravenous injection.

Because fatal reactions often resembling anaphylaxis have been reported with protamine, it should be given only when resuscitation techniques and treatment of anaphylactoid shock are readily available. For additional information consult the labeling of Protamine Sulfate Injection.

11 DESCRIPTION

Heparin is a heterogeneous group of straight-chain anionic mucopolysaccharides, called glycosaminoglycans, possessing anticoagulant properties. It is composed of polymers of alternating derivations of α-D-glucosamido (N-sulfated O-sulfated O-sulfated or N-acetylated) and O-sulfated uronic acid (α-L-iduronic acid or β-D-glucoronic acid). Structure of heparin sodium (representative subunits):

Heparin Sodium Injection, USP is a sterile solution of heparin sodium derived from porcine intestinal mucosa, standardized for anticoagulant activity. It is to be administered by intravenous or deep subcutaneous routes. The potency is determined by a biological assay using a USP reference standard based on units of heparin activity per milligram. Each 0.5 mL of Heparin Sodium Injection, USP contains:

Heparin Sodium | Sodium Chloride
5,000 USP units | 2.5 mg

pH 5.0-7.5; sodium hydroxide and/or hydrochloric acid added, if needed, for pH adjustment.

12 CLINICAL PHARMACOLOGY

12.1 Mechanism of Action

Heparin interacts with the naturally occurring plasma protein, Antithrombin III, to induce a conformational change, which markedly enhances the serine protease activity of Antithrombin III, thereby inhibiting the activated coagulation factors involved in the clotting sequence, particularly Xa and IIa. Small amounts of heparin inhibit Factor Xa, and larger amounts inhibit thrombin (Factor IIa). Heparin also prevents the formation of a stable fibrin clot by inhibiting the activation of the fibrin stabilizing factor. Heparin does not have fibrinolytic activity; therefore, it will not lyse existing clots.

12.2 Pharmacodynamics

Various times (activated clotting time, activated partial thromboplastin time, prothrombin time, whole blood clotting time) are prolonged by full therapeutic doses of heparin; in most cases, they are not measurably affected by low doses of heparin. The bleeding time is usually unaffected by heparin.

12.3 Pharmacokinetics

Absorption

Heparin is not absorbed through the gastrointestinal tract and therefore administered via parenteral route. Peak plasma concentration and the onset of action are achieved immediately after intravenous administration.

Distribution

Heparin is highly bound to antithrombin, fibrinogens, globulins, serum proteases and lipoproteins. The volume of distribution is 0.07 L/kg.

Elimination

Metabolism

Heparin does not undergo enzymatic degradation.

Excretion

Heparin is mainly cleared from the circulation by liver and reticuloendothelial cells mediated uptake into extravascular space. Heparin undergoes biphasic clearance, a) rapid saturable clearance (zero order process due to binding to proteins, endothelial cells and macrophage) and b) slower first order elimination. The plasma half-life is dose-dependent and it ranges from 0.5 to 2 h.

Specific Populations

Geriatric patients

Patients over 60 years of age, following similar doses of heparin, may have higher plasma levels of heparin and longer activated partial thromboplastin times (APTTs) compared with patients under 60 years of age [see Use in Specific Populations (8.5)].

13 NONCLINICAL TOXICOLOGY

13.1 Carcinogenesis, Mutagenesis, Impairment of Fertility

No long-term studies in animals have been performed to evaluate carcinogenic potential of heparin. Also, no reproduction studies in animals have been performed concerning mutagenesis or impairment of fertility.

16 HOW SUPPLIED/STORAGE AND HANDLING

Heparin Sodium Injection, USP is a preservative-free clear solution available as:

Product Code | Unit of Sale | Strength | Each
761805 | NDC 63323-118-05 Unit of 24 | 5,000 USP units per 0.5 mL (10,000 USP units per mL) | NDC 63323-118-01 0.5 mL fill in 1 mL prefilled single dose syringe

Discard unused portion

Store at 20°-25°C (68°-77°F) [See USP Controlled Room Temperature].

Protect from freezing.

Do not place syringe on a sterile field.

17 PATIENT COUNSELING INFORMATION

Hemorrhage

Inform patients that it may take them longer than usual to stop bleeding, that they may bruise and/or bleed more easily when they are treated with heparin, and that they should report any unusual bleeding or bruising to their physician. Hemorrhage can occur at virtually any site in patients receiving heparin. Fatal hemorrhages have occurred [see Warnings and Precautions (5.2)].

Prior to Surgery

Advise patients to inform physicians and dentists that they are receiving heparin before any surgery is scheduled [see Warnings and Precautions (5.2)].

Heparin-Induced Thrombocytopenia

Inform patients of the risk of heparin-induced thrombocytopenia (HIT). HIT may progress to the development of venous and arterial thromboses, a condition known as heparin-induced thrombocytopenia and thrombosis (HITT). HIT and HITT can occur up to several weeks after the discontinuation of heparin therapy [see Warnings and Precautions (5.3)].

Hypersensitivity

Inform patients that generalized hypersensitivity reactions have been reported. Necrosis of the skin has been reported at the site of subcutaneous injection of heparin [see Warnings and Precautions (5.8), Adverse Reactions (6.1)].

Other Medications

Because of the risk of hemorrhage, advise patients to inform their physicians and dentists of all medications they are taking, including non-prescription medications, and before starting any new medication [see Drug Interactions (7.1)].

For more information concerning this drug, please call Fresenius Kabi USA, LLC at 1-800-551-7176.

To report SUSPECTED ADVERSE REACTIONS, contact Fresenius Kabi USA, LLC at 1-800-551-7176 or FDA at 1-800-FDA-1088 or www.fda.gov/medwatch.

The brand names mentioned in this document are the trademarks of their respective owners.

Lake Zurich, IL 60047 www.fresenius-kabi.com/us
451614

PACKAGE LABEL

Principal Display Panel – Heparin 0.5 mL Single-Dose Carton Label

Rx only

NDC 63323-118-05

Heparin
Sodium Injection, USP

5,000 USP units
per 0.5 mL

NOT for lock flush

For Intravenous or Subcutaneous Use.

Derived from Porcine Intestinal Mucosa

Do NOT place syringe on a Sterile Field.

24 x 0.5 mL Prefilled Single-Dose Syringes

Discard unused portion.

PACKAGE LABEL

Principal Display Panel – Heparin 0.5 mL Single-Dose Print Mat Label

Rx only

NDC 63323-118-01

Heparin
Sodium Injection, USP

5,000 USP units
per 0.5 mL

NOT for lock flush

For Intravenous or Subcutaneous Use.

0.5 mL Prefilled Single-Dose Syringe

PACKAGE LABEL

Principal Display Panel – Heparin 0.5 mL Single-Dose Syringe Label

For IV or Subcutaneous Use. 0.5 mL Prefilled
Single-Dose Syringe. From Porcine Intestines

NOT for lock flush

Rx only

Heparin
Sodium Injection, USP

5,000 USP units
per 0.5 mL